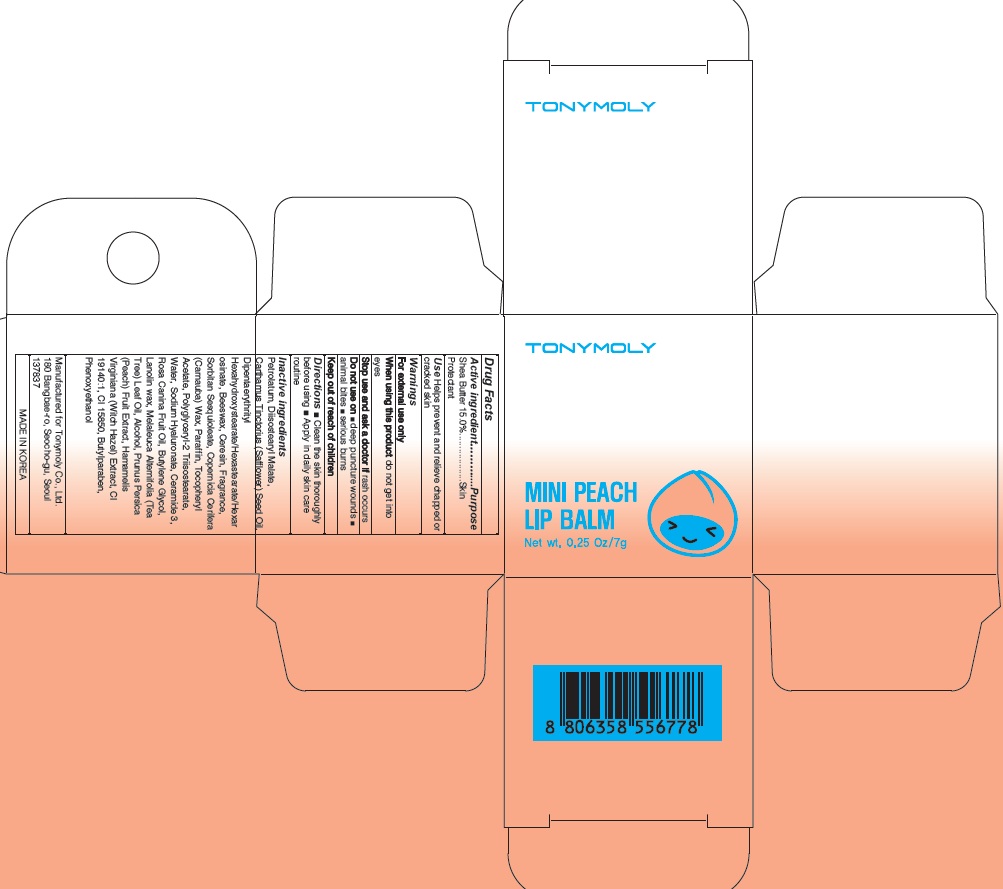 DRUG LABEL: MINI PEACH LIP BALM
NDC: 59078-315 | Form: CREAM
Manufacturer: TONYMOLY CO.,LTD
Category: otc | Type: HUMAN OTC DRUG LABEL
Date: 20160630

ACTIVE INGREDIENTS: Shea Butter 1.05 g/7 g
INACTIVE INGREDIENTS: Petrolatum; Diisostearyl Malate

ACTIVE INGREDIENT

Active ingredient: Shea Butter 15.0%

INACTIVE INGREDIENT

Inactive Ingredient: Petrolatum, Diisostearyl Malate, Carthamus Tinctorius (Safflower) Seed Oil, Dipentaerythrityl Hexahydroxystearate/Hexastearate/Hexarosinate, Beeswax, Ceresin, Fragrance, Sorbitan Sesquioleate, Copernicia Cerifera (Carnauba) Wax, Paraffin, Tocopheryl Acetate, Polyglyceryl-2 Triisostearate, Water, Sodium Hyaluronate, Ceramide 3, Rosa Canina Fruit Oil, Butylene Glycol, Lanolin wax, Melaleuca Alternifolia (Tea Tree) Leaf Oil, Alcohol, Prunus Persica (Peach) Fruit Extract, Hamamelis Virginiana (Witch Hazel) Extract, CI 19140:1, CI 15850, Butylparaben, Phenoxyethanol

PURPOSE

Purpose: Skin Protectant

WARNINGS

Warnings: For external use only When using this product do not get into eyes Stop use and ask a doctor if rash occurs Do not use on - deep puncture wounds - animal bites - serious burns Keep out of reach of children

KEEP OUT OF REACH OF CHILDREN

Use

Use: Helps prevent and relieve chapped or cracked skin

Directions

Directions: - Clean the skin thoroughly before using - Apply in daily skin care routine